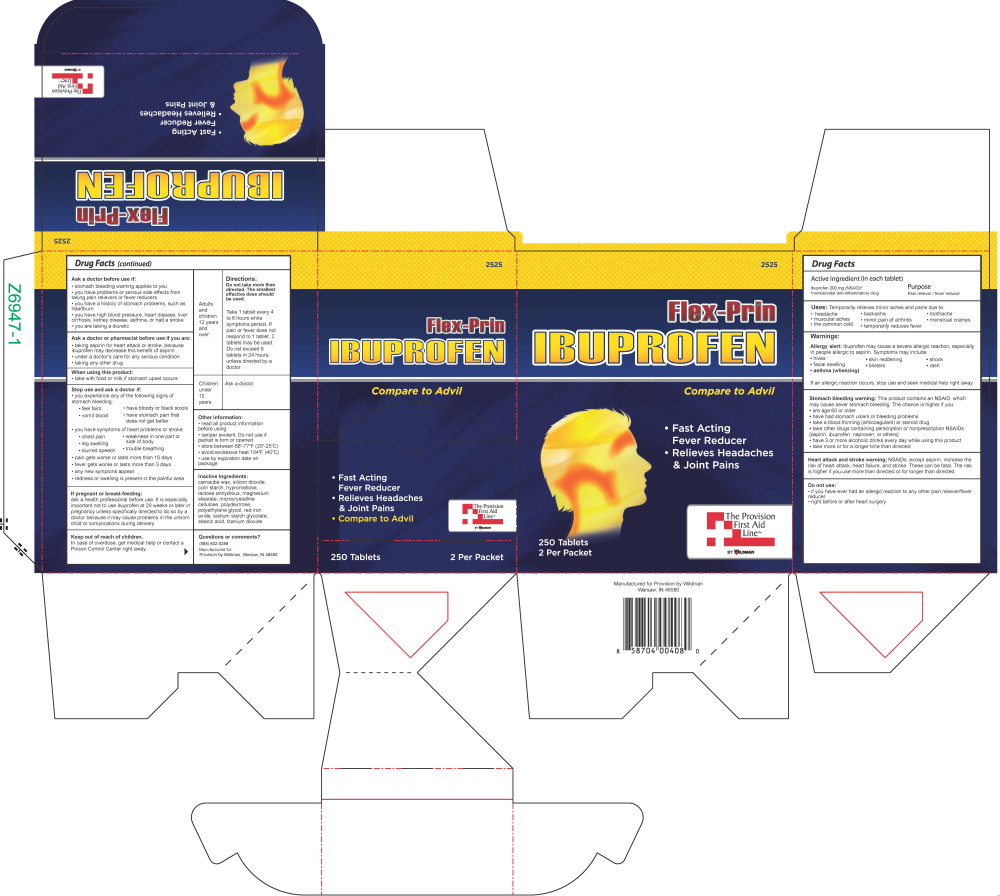 DRUG LABEL: Ibuprofen
NDC: 84269-2525 | Form: TABLET
Manufacturer: Wildman Business Group
Category: otc | Type: HUMAN OTC DRUG LABEL
Date: 20240819

ACTIVE INGREDIENTS: Ibuprofen 200 mg/1 1
INACTIVE INGREDIENTS: CARNAUBA WAX; SILICON DIOXIDE; STARCH, CORN; HYPROMELLOSE, UNSPECIFIED; ANHYDROUS LACTOSE; MAGNESIUM STEARATE; MICROCRYSTALLINE CELLULOSE; POLYDEXTROSE; POLYETHYLENE GLYCOL, UNSPECIFIED; FERRIC OXIDE RED; SODIUM STARCH GLYCOLATE TYPE A POTATO; STEARIC ACID; TITANIUM DIOXIDE

Active Ingredient (in each tablet)

Ibuprofen 200 mg (NSAID)*

*nonsteroidal anti-inflammatory drug

Purpose

Pain reliever / fever reducer

Uses:

Temporarily relieves minor aches and pains due to:

- headache
- muscular aches
- the common cold
- backache
- minor pain of arthritis
- temporarily reduces fever
- toothache
- menstrual cramps

Warnings:

Allergy alert: Ibuprofen may cause a severe allergic reaction, especially in people allergic to aspirin. Symptoms may include:

- hives
- facial swelling
- asthma (wheezing)
- skin reddening
- shock
- rash
- blisters

If an allergic reaction occurs, stop use and seek medical help right away.

Stomach bleeding warning: This product contains an NSAID, which may cause severe stomach bleeding. The chance is higher if you:

- are age 60 or older
- have had stomach ulcers or bleeding problems
- take a blood thinning (anticoagulant) or steroid drug
- take other drugs containing prescription or nonprescription NSAIDs [aspirin, ibuprofen, naproxen, or others]
- have 3 or more alcoholic drinks every day while using this product
- take more or for a longer time than directed

Heart attack and stroke warning: NSAIDs, except aspirin, increase the risk of heart attack, heart failure, and stroke. These can be fatal. The risk is higher if you use more than directed or for longer than directed.

Do not use:

- if you have ever had an allergic reaction to any other pain reliever/fever reducer
- right before or after heart surgery

Ask a doctor before use if:

- stomach bleeding warning applies to you
- you have problems or serious side effects from taking pain relievers or fever reducers
- you have a history of stomach problems, such as heartburn
- you have high blood pressure, heart disease, liver cirrhosis, kidney disease, asthma, or had a stroke
- you are taking a diuretic

Ask a doctor or pharmacist before use if you are:

- taking aspirin for heart attack or stroke, because ibuprofen may decrease this benefit of aspirin
- under a doctor's care for any serious condition
- taking any other drug

When using this product:

- take with food or milk if stomach upset occurs

Stop use and ask a doctor if:

- you experience any of the following signs of stomach bleeding:
  - feel faint
  - vomit blood
  - have bloody or black stools
  - have stomach pain that does not get better
- you have symptoms of heart problems or stroke:
  - chest pain
  - weakness in one part or side of body
  - leg swelling
  - slurred speech
  - trouble breathing
- pain gets worse or lasts more than 10 days
- fever gets worse or lasts more than 3 days
- any new symptoms appear
- redness or swelling is present in the painful area

If pregnant or breast-feeding:

ask a health professional before use. It is especially important not to use ibuprofen at 20 weeks or later in pregnancy unless specifically directed to do so by a doctor because it may cause problems in the unborn child or complications during delivery.

Keep out of reach of children.

In case of overdose, get medical help or contact a Poison Control Center right away.

DIRECTIONS

Adults and children 12 years and over:

- do not take more than directed
- the smallest effective dose should be used
- take 1 tablet every 4 to 6 hours while symptoms persist
  - if pain or fever does not respond to 1 tablet, 2 tablets may be used
  - do not exceed 6 tablets in 24 hours, unless directed by a doctor

Children under 12 years: ask a doctor

OTHER INFORMATION

- read all product information before using
- tamper evident. Do not use if packet is torn or opened
- store between 68°-77°F (20°-25°C)
- avoid excessive heat 104°F (40°C)
- use by expiration date on package

Inactive Ingredients

carnauba wax, silicon dioxide, corn starch, hypromellose, lactose anhydrous, magnesium stearate, microcrystalline cellulose, polydextrose, polyethylene glycol, red iron oxide, sodium starch glycolate, stearic acid, titanium dioxide

Principal Display Panel – 250 Tablet Box Label

2525

Flex-Prin

Ibuprofen

Compare to Advil

- Fast Acting Fever Reducer
- Relieves Headaches & Joint Pains
- Compare to Advil

The Provision

First Aid

Line™

BY WILDMAN